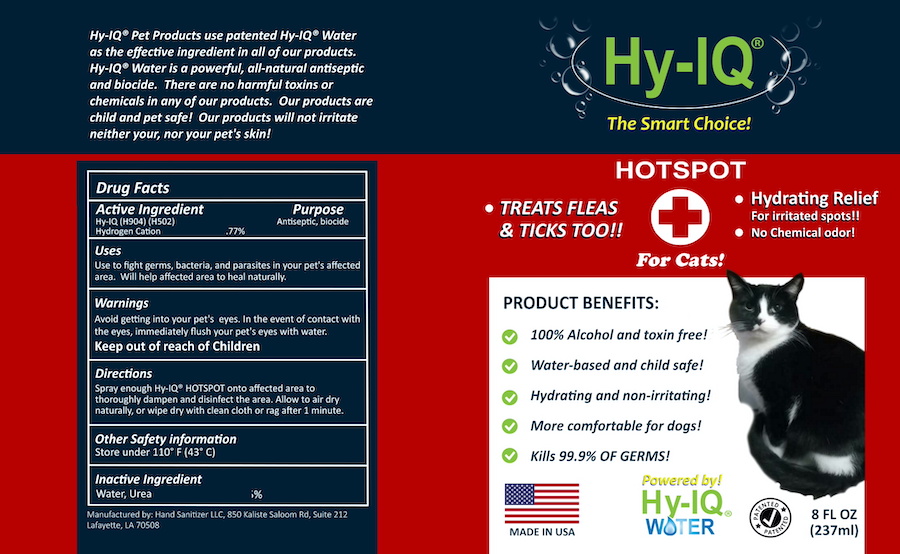 DRUG LABEL: HY IQ HOT SPOT TREATMENT FOR CATS
NDC: 76701-217 | Form: SPRAY
Manufacturer: HAND SANITIZER LLC
Category: animal | Type: OTC ANIMAL DRUG LABEL
Date: 20210625

ACTIVE INGREDIENTS: HYDROGEN CATION 10 mg/1 mL
INACTIVE INGREDIENTS: WATER 940 mg/1 mL; UREA 50 mg/1 mL

HY IQ HOT SPOT TREATMENT FOR CATS

ACTIVE INGREDIENT

HY-IQ WATER ([H9O4] | [H502])

HYDROGEN CATION .77%

PURPOSE

ANTISEPTIC

USES

USE TO FIGHT GERMS, BACTERIA AND PARASITES IN YOUR PET'S AFFECTED AREA. WILL HELP AFFECTED AREA TO HEAL NATURALLY.

WARNINGS

AVOID GETTING INTO YOUR PET'S EYES. IN THE EVENT OF CONTACT WITH THE EYES, IMMEDIATELY FLUSH YOUR PET'S EYES WITH WATER.

KEEP OUT OF REACH OF CHILDREN

DIRECTIONS

SPRAY ENOUGH HY-IQ® HOTSPOT ONTO AFFECTED AREA TO THOROUGHLY DAMPEN AND DISINFECT THE AREA. ALLOW TO AIR DRY NATURALLY, OR WIPE DRY WITH CLEAN CLOTH OR RAG AFTER 1 MINUTE.

OTHER SAFETY INFORMATION

STORE UNDER 110° F (43°C)

INACTIVE INGREDIENTS

WATER, UREA